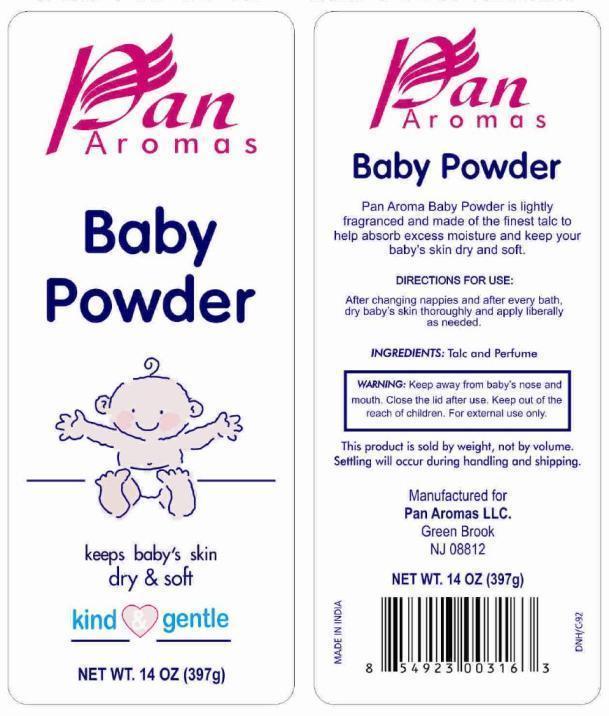 DRUG LABEL: Pan Aromas Baby
NDC: 50346-004 | Form: POWDER
Manufacturer: Pan Aromas LLC
Category: otc | Type: HUMAN OTC DRUG LABEL
Date: 20121219

ACTIVE INGREDIENTS: TALC 1 g/1 g

Active Ingredient

Talc 100%

Purpose

Skin Protectant

Uses

To help absorb excess moisture and keep your baby's skin dry and soft.

Warnings

For external use only.

Keep away from baby's nose and mouth. Close lid after use.

Keep out of the reach of children

Children if swallowed get medical help or contact Poison Control Center right away.

Directions

After changing nappies and after every bath, dry baby's skin thoroughly and apply liberally as needed

Inactive Ingredient

Fragrance

PRINCIPAL DISPLAY PANEL

Pan Aromas Baby Powder

NET WT. 14 OZ (397g)